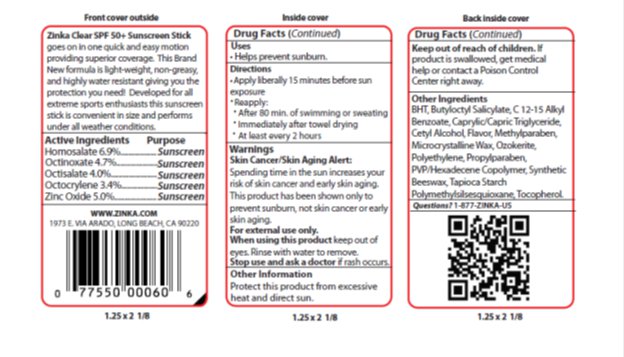 DRUG LABEL: Zinka SPF 50 Facestick
NDC: 52993-150 | Form: STICK
Manufacturer: Zinka
Category: otc | Type: HUMAN OTC DRUG LABEL
Date: 20140509

ACTIVE INGREDIENTS: OCTINOXATE 4.7 mg/1 g; HOMOSALATE 6.90 mg/1 g; OCTISALATE 4 mg/1 g; OCTOCRYLENE 3.40 mg/1 g; ZINC OXIDE 5 mg/1 g
INACTIVE INGREDIENTS: MICROCRYSTALLINE WAX 10.50 mg/1 g; CERESIN 10.30 mg/1 g; MEDIUM-CHAIN TRIGLYCERIDES 15.5 mg/1 g; ALKYL (C12-15) BENZOATE 13 mg/1 g; WHITE WAX 6.3 mg/1 g

Drug Facts

Active ingredient

Homosalate (6.9%), Octinoxate (4.7%), Octisalate (4.0%), Octocrylene (3.4%), Zinc Oxide (5.0%)

Purpose

Sunscreen

Keep Out of Reach of Children

If swallowed get medical help or contact a Poison Control Center right away.

Uses

Helps prevent sunburn.

Warnings

Skin Cancer/Skin Aging Alert: Spending time in the sun increases your risk of skin cancer and early skin aging. This product has been shown only to prevent sunburn, not skin cancer or early aging.

For external use only: Stop use and ask a doctor: if rash or irritation develops and lasts. Keep out of eyes. Rinse with water to remove.

Directions

Apply liberally 15 minutes before sun exposure. Reapply: After 80 minutes of swimming or sweating. Immediately after towel drying. At least every 2 hours.

Inactive Ingredients

BHT, Butyloctyl Salicylate, C12-15 Alkyl Benzoate, Caprylic/Capric Triglyceride, Cetyl Alcohol, Flavor Methylparaben, Microcrystalline Wax, Ozokerite, Polyethylene, Propylparaben, PVP/Hexadecene Copolymer, Synthetic Beeswax, Tapioca Starch Polymethylsilsesquioxane, Tocopherol,.